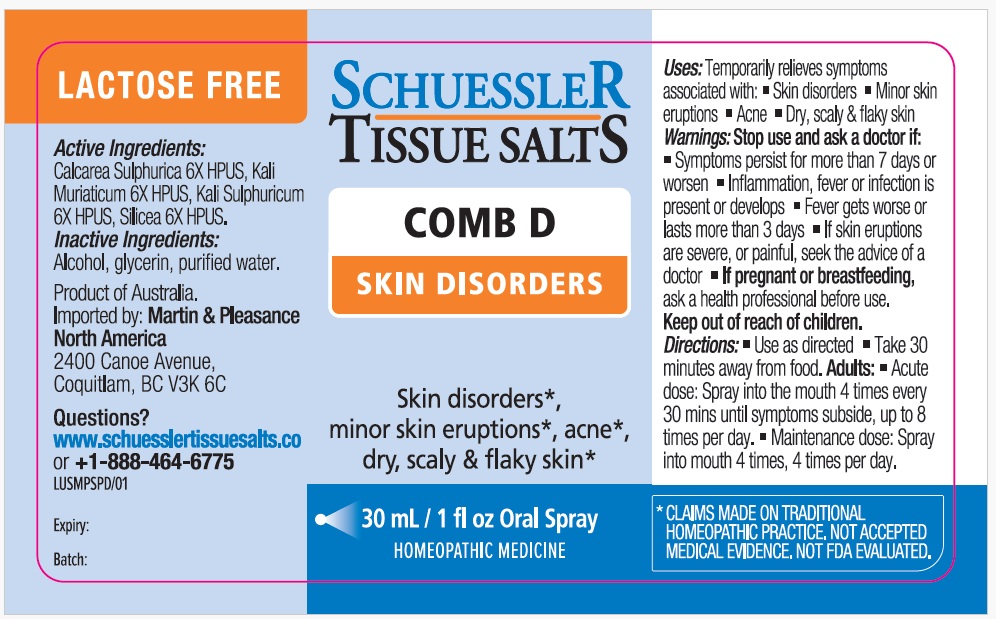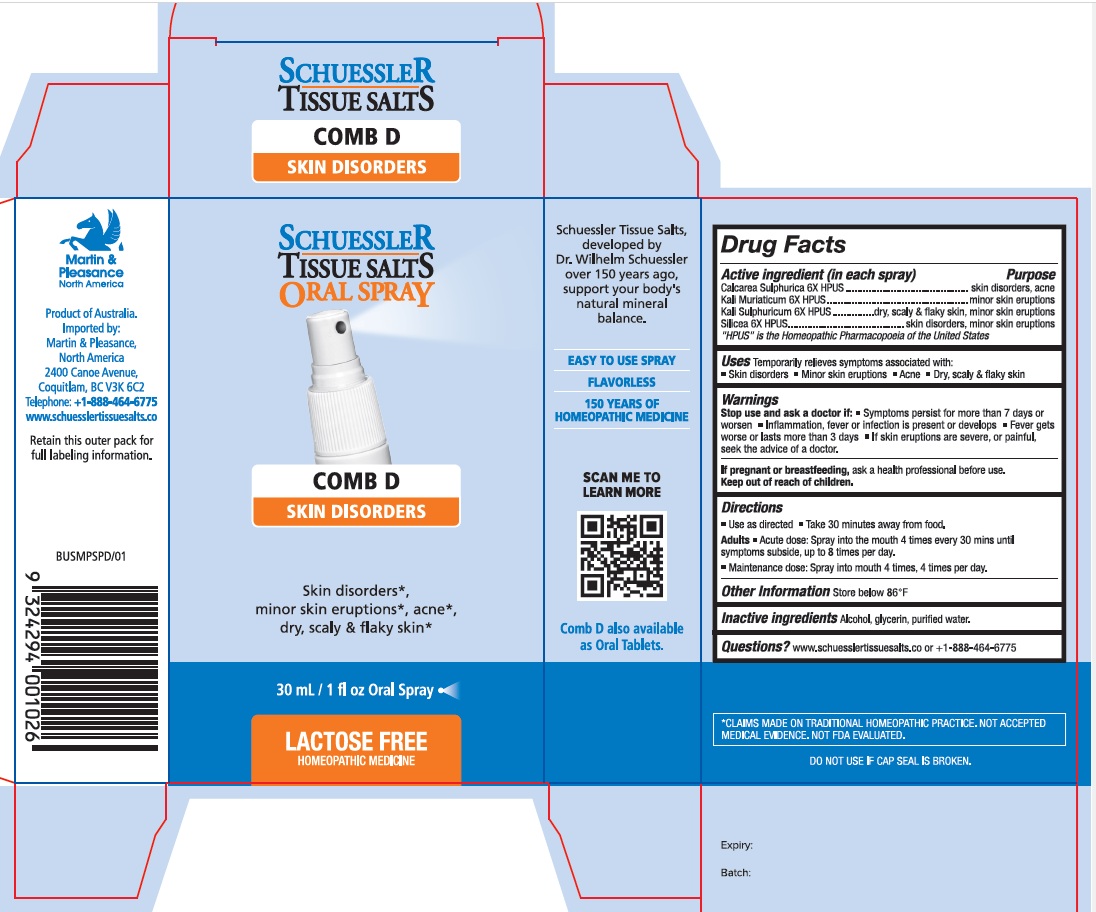 DRUG LABEL: Schuessler Tissue Salts Comb D Skin Disorders
NDC: 84999-028 | Form: SPRAY
Manufacturer: Martin & Pleasance Pty Ltd
Category: homeopathic | Type: HUMAN OTC DRUG LABEL
Date: 20250813

ACTIVE INGREDIENTS: POTASSIUM CHLORIDE 6 [hp_X]/30 mL; POTASSIUM SULFATE 6 [hp_X]/30 mL; CALCIUM SULFATE DIHYDRATE 6 [hp_X]/30 mL; SILICON DIOXIDE 6 [hp_X]/30 mL
INACTIVE INGREDIENTS: ALCOHOL; GLYCERIN; WATER

Active ingredient (in each spray) Purpose

Calcarea Sulphurica 6X HPUS ............................................ skin disorders, acne
Kali Muriaticum 6X HPUS ................................................... minor skin eruptions
Kali Sulphuricum 6X HPUS ............... dry, scaly & flaky skin, minor skin eruptions
Silicea 6X HPUS .......................................... skin disorders, minor skin eruptions

"HPUS" is the Homeopathic Pharmacopoeia of the United States

Uses

Temporarily relieves symptoms associated with:

- Skin disorders
- Minor skin eruptions
- Acne
- Dry, scaly & flaky skin

Warnings

Slop use and ask a doctor if:

• Symptoms persist for more than 7 days or worsen

• Inflammation, fever, or infection is present or develops

• Fever gets worse or lasts more than 3 days

• If skin eruptions are severe or painful, seek the advice of a doctor.

If pregnant or breastfeeding, ask a health professional before use. Keep out of reach of children.

Directions

- Use as directed
- Take 30 minutes away from food.

Adults

- Acute dose: Spray into the mouth 4 times every 30 mins until symptoms subside, up to 8 times per day.
- Maintenance dose: Spray into mouth 4 times, 4 times per day.

Other Information

Store below 86°F

Inactive Ingredients

Alcohol, Glycerin, Purified Water

Questions?www.schuesslertissuesalts.co or + 1-888-464-6775